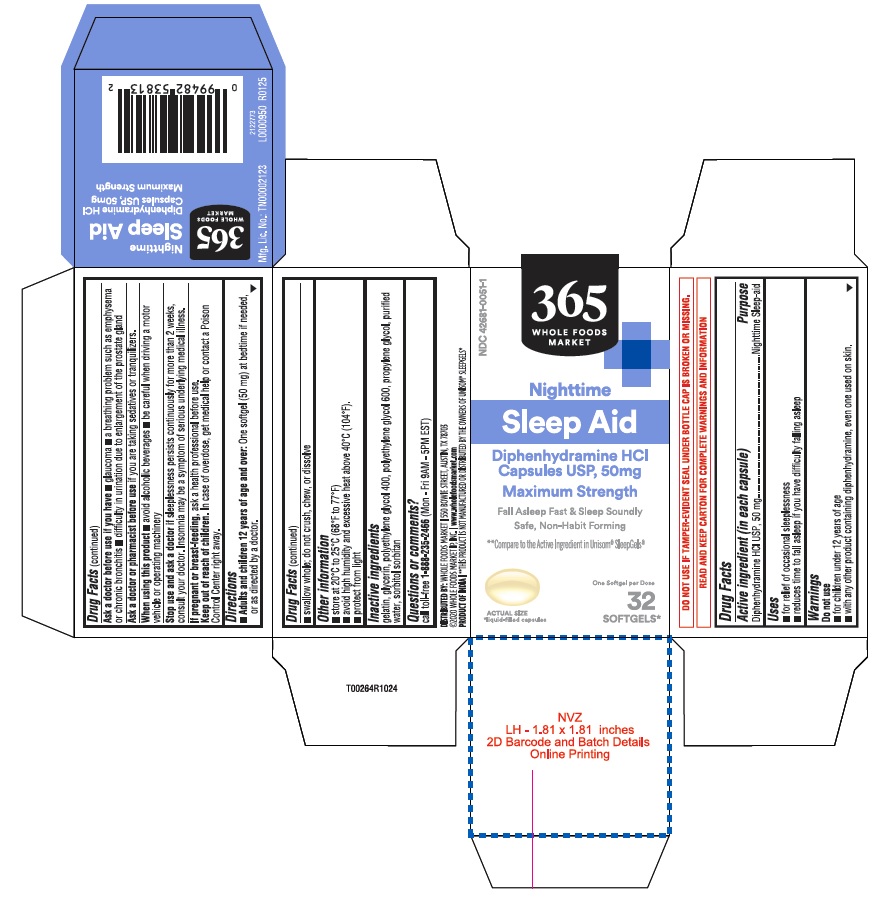 DRUG LABEL: Nighttime Sleep-Aid
NDC: 42681-0051 | Form: CAPSULE, LIQUID FILLED
Manufacturer: Whole Foods Market, INC.
Category: otc | Type: HUMAN OTC DRUG LABEL
Date: 20251201

ACTIVE INGREDIENTS: DIPHENHYDRAMINE HYDROCHLORIDE 50 mg/1 1
INACTIVE INGREDIENTS: POLYETHYLENE GLYCOL 600; SORBITAN; GELATIN; POLYETHYLENE GLYCOL 400; WATER; GLYCERIN; PROPYLENE GLYCOL; SORBITOL

whole foods-Diphenhydramine HCl Capsules, 50 mg dye free

Active ingredient (in each capsule)

Diphenhydramine HCl 50 mg

Purpose

Nighttime sleep-aid

Uses

■ for relief of occasional sleeplessness ■ reduces time to fall asleep if you have difficulty falling asleep

Warnings

Do not use

■ for children under 12 years of age

■ with any other product containing diphenhydramine, even one used on skin.

Ask a doctor before use if you have

■ glaucoma ■ a breathing problem such as emphysema or chronic bronchitis

■ difficulty in urination due to enlargement of the prostate gland

Ask a doctor or pharmacist before use

if you are taking sedatives or tranquilizers.

When using this product

■ avoid alcoholic beverages ■ be careful when driving a motor vehicle or operating machinery

Stop use and ask a doctor if

sleeplessness persists continuosly for more than 2 weeks, consult your doctor. Insomnia may be a symptom of serious underlying medical illness.

If pregnant or breast- feeding,

ask a health professional before use.

Keep out of reach of children.

In case of overdose, get medical help or contact a Poison Control Center right away.

Directions

■ Adults and children 12 years of age and over:One softgel (50 mg) at bedtime if needed, or as directed by a doctor.
■ swallow whole; do not crush, chew, or dissolve

Other information

■ store at 20°C to 25°C (68°F to 77°F) ■ avoid high humidity and excessive heat above 40°C (104°F).
■ protect from light

Inactive ingredients

gelatin, glycerin, polyethylene glycol 400, polyethylene glycol 600, propylene glycol, purified water, sorbitol sorbitan solution

Questions or comments?

call toll-free 1-888-235-2466 (Mon - Fri 9AM - 5PM EST)

DO NOT USE IF TAMPER-EVIDENT SEAL UNDER BOTTLE CAP IS BROKEN OR MISSING.

READ AND KEEP CARTON FOR COMPLETE WARNINGS AND INFORMATION

DISTRIBUTED BY: WHOLE FOODS MARKET I 550 BOWIE STREET, AUSTIN, TX 78703
©2020 WHOLE FOODS MARKET IP, INC. I www.wholefoodsmarket.com
PRODUCT OF INDIAI**THIS PRODUCT IS NOT MANUFACTURED OR DISIRIBUTED BY THE OWNERS OF UNISOM® SLEEPGELS®

L0000950 R0125

Mfg. Lic. No.: TN00002123

Lot No.:

Exp. Date:

32s count

NDC 42681-0051-1

365

WHOLE FOODS

MARKET

Nighttime

Sleep-Aid

Diphenhydramine HCl

Capsules USP, 50 mg

Maximum Strength

Fall asleep fast & Sleep Soundly

safe, non habit-forming

**Compare to the Active Ingredient in Unisom® SleepGels®

One softgel per dose

32

SOFTGELS*

*Liquid-filled capsules